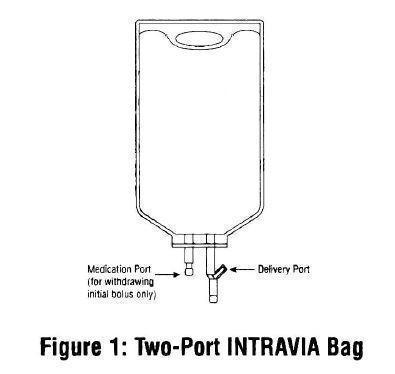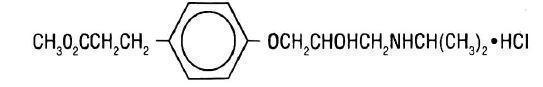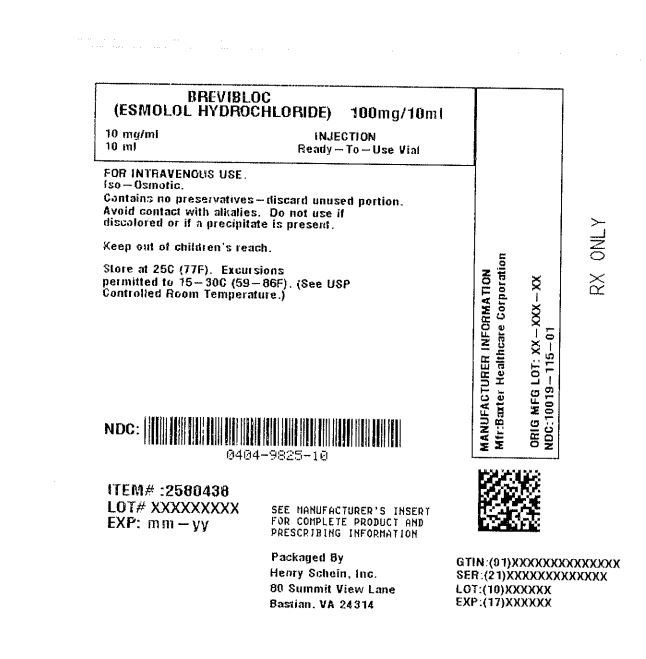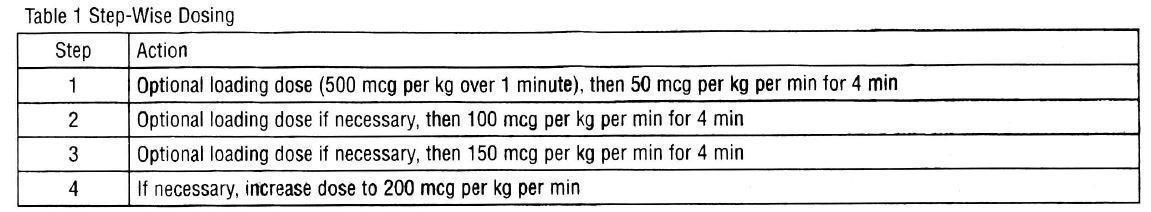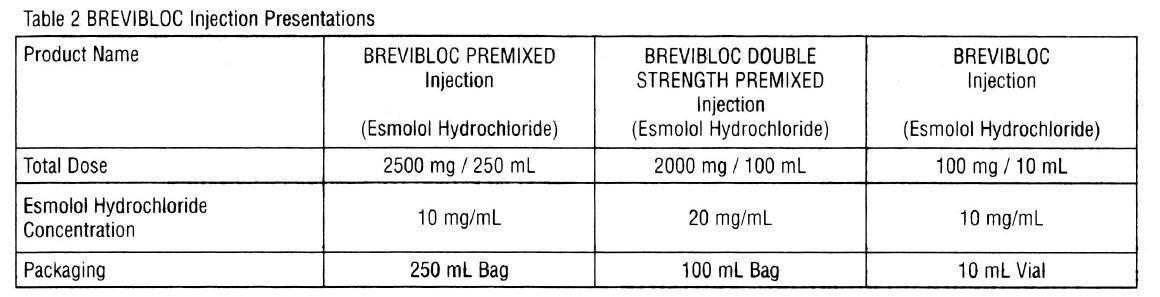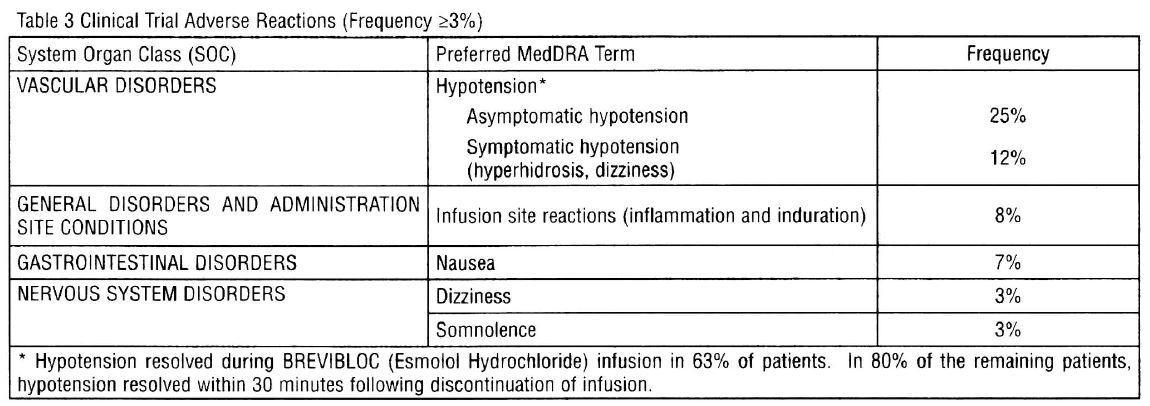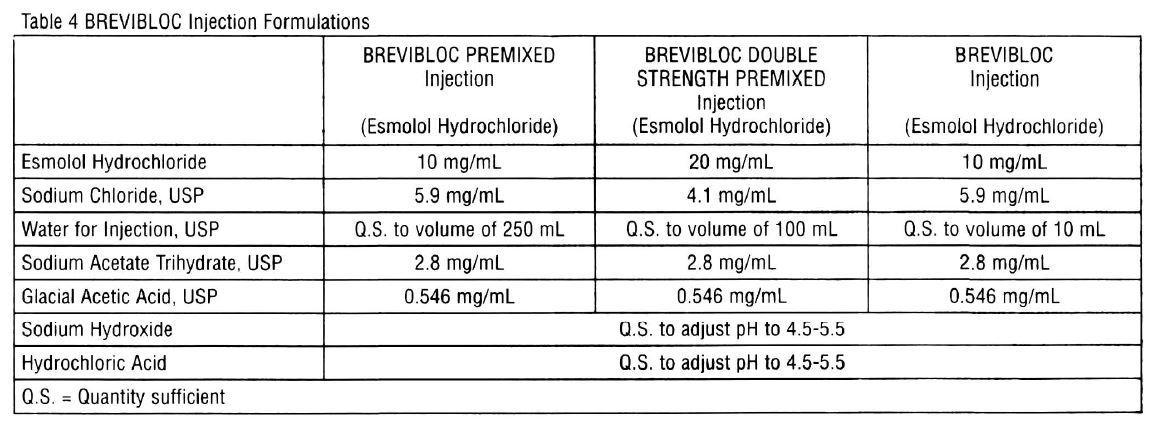 DRUG LABEL: Brevibloc
NDC: 0404-9825 | Form: INJECTION
Manufacturer: Henry Schein, Inc
Category: prescription | Type: HUMAN PRESCRIPTION DRUG LABEL
Date: 20251027

ACTIVE INGREDIENTS: Esmolol Hydrochloride 10 mg/1 mL

HIGHLIGHTS OF PRESCRIBING INFORMATION

Brevibloc (Esmolol Hydrochloride) 10 mg/mL Injection 10 mL Single Dose Vial
These highlights do not include all the information needed to use BREVIBLOC safely and effectively. See full prescribing information for BREVIBLOC injection.
BREVIBLOC (Esmolol Hydrochloride) injection, for intravenous use
Initial U.S. Approval: 1986

1 INDICATIONS AND USAGE

BREVIBLOC injection is a beta adrenergic blocker indicated for the short-term treatment of:

- Control of ventricular rate in supraventricular tachycardia including atrial fibrillation and atrial flutter and control of heart rate in noncompensatory sinus tachycardia (1.1)
- Control of perioperative tachycardia and hypertension (1.2)

2 DOSAGE AND ADMINISTRATION

- Administer intravenously (2.1, 2.2)
- Titrate using ventricular rate or blood pressure at ≥4-minute intervals. (2.1, 2.2)
- Supraventricular tachycardia (SVT) or noncompensatory sinus tachycardia (2.1)
  - Optional loading dose: 500 mcg per kg infused over one minute
  - Then 50 mcg per kg per minute for the next 4 minutes
  - Adjust dose as needed to a maximum of 200 mcg per kg per minute.
  - Additional loading doses may be administered
- Perioperative tachycardia or hypertension (2.2)
  - Loading dose: 500 mcg per kg over 1 minute for gradual control (1 mg per kg over 30 seconds for immediate control)
  - Then 50 mcg per kg per min infusion for gradual control (150 mcg per kg per minute for immediate control) adjusted to a maximum of 200 (tachycardia) or 300 (hypertension) mcg per kg per min (2.2)

3 DOSAGE FORMS AND STRENGTHS

- Injection: 100 mg/10 mL (10 mg/mL) in 10 mL vial (3)
- Injection: 2500 mg/250 mL (10 mg/mL) in 250 mL Premixed Injection bag (3)
- Injection: 2000 mg/100 mL (20 mg/mL) in 100 mL Double Strength Premixed Injection bag (3)

4 CONTRAINDICATIONS

- Severe sinus bradycardia (4)
- Heart block greater than first degree (4)
- Sick sinus syndrome (4)
- Decompensated heart failure (4)
- Cardiogenic shock (4)
- Coadministration of IV cardiodepressant calcium-channel antagonists (e.g. verapamil) in close proximity to BREVIBLOC injection (4, 7)
- Pulmonary hypertension (4)
- Known hypersensitivity to esmolol (4)

5 WARNINGS AND PRECAUTIONS

- Risk of hypotension, bradycardia, and cardiac failure: Monitor for signs and symptoms of cardiovascular adverse effects. Reduce or discontinue use (5.1, 5.2, 5.3, 5.10)
- Risk of exacerbating reactive airway disease (5.5)
- Diabetes mellitus: Increases the effect of hypoglycemic agents and masks hypoglycemic tachycardia (5.6)
- Risk of unopposed alpha-agonism and severe hypertension in untreated pheochromocytoma (5.9)
- Risk of myocardial ischemia when abruptly discontinued in patients with coronary artery disease (5.12, 5.15)

6 ADVERSE REACTIONS

Most common adverse reactions (incidence >10%) are symptomatic hypotension (hyperhidrosis, dizziness) and asymptomatic hypotension (6)

To report SUSPECTED ADVERSE REACTIONS, contact Baxter Healthcare Corporation at 1-866-888-2472 or FDA at 1-800-FDA-1088 or www.fda.gov/medwatch.

7 DRUG INTERACTIONS

- Digitalis glycosides: Risk of bradycardia (7)
- Anticholinesterases: Prolongs neuromuscular blockade (7)
- Antihypertensive agents: Risk of rebound hypertension (7)
- Sympathomimetic drugs: Dose adjustment needed (7)
- Vasoconstrictive and positive inotropic effect substances: Avoid concomitant use (7)

FULL PRESCRIBING INFORMATION

1 INDICATIONS AND USAGE

1.1 Supraventricular Tachycardia or Noncompensatory Sinus Tachycardia

BREVIBLOC (Esmolol Hydrochloride) is indicated for the rapid control of ventricular rate in patients with atrial fibrillation or atrial flutter in perioperative, postoperative, or other emergent circumstances where short term control of ventricular rate with a short-acting agent is desirable. BREVIBLOC is also indicated in noncompensatory sinus tachycardia where, in the physician's judgment, the rapid heart rate requires specific intervention. BREVIBLOC is intended for short-term use.

1.2 Intraoperative and Postoperative Tachycardia and/or Hypertension

BREVIBLOC (Esmolol Hydrochloride) is indicated for the short-term treatment of tachycardia and hypertension that occur during induction and tracheal intubation, during surgery, on emergence from anesthesia and in the postoperative period, when in the physician's judgment such specific intervention is considered indicated.

Use of BREVIBLOC to prevent such events is not recommended.

2 DOSAGE AND ADMINISTRATION

2.1 Dosing for the Treatment of Supraventricular Tachycardia or Noncompensatory Sinus Tachycardia

BREVIBLOC is administered by continuous intravenous infusion with or without a loading dose. Additional loading doses and/or titration of the maintenance infusion (step-wise dosing) may be necessary based on desired ventricular response.

In the absence of loading doses, continuous infusion of a single concentration of esmolol reaches pharmacokinetic and pharmacodynamic steady-state in about 30 minutes.

The effective maintenance dose for continuous and step-wise dosing is 50 to 200 mcg per kg per minute, although doses as low as 25 mcg per kg per minute have been adequate. Dosages greater than 200 mcg per kg per minute provide little added heart rate lowering effect, and the rate of adverse reactions increases.

Maintenance infusions may be continued for up to 48 hours.

2.2 Intraoperative and Postoperative Tachycardia and Hypertension

In this setting it is not always advisable to slowly titrate to a therapeutic effect. Therefore two dosing options are presented: immediate control and gradual control.

Immediate Control

- Administer 1 mg per kg as a bolus dose over 30 seconds followed by an infusion of 150 mcg per kg per min if necessary.
- Adjust the infusion rate as required to maintain desired heart rate and blood pressure. Refer to Maximum Recommended Doses below.

Gradual Control

- Administer 500 mcg per kg as a bolus dose over 1 minute followed by a maintenance infusion of 50 mcg per kg per min for 4 minutes.
- Depending on the response obtained, continue dosing as outlined for supraventricular tachycardia. Refer to Maximum Recommended Doses below.

Maximum Recommended Doses

- For the treatment of tachycardia, maintenance infusion dosages greater than 200 mcg per kg per min are not recommended; dosages greater than 200 mcg per kg per min provide little additional heart rate-lowering effect, and the rate of adverse reactions increases.
- For the treatment of hypertension, higher maintenance infusion dosages (250-300 mcg per kg per min) may be required. The safety of doses above 300 mcg per kg per minute has not been studied.

2.3 Transition from BREVIBLOC Injection Therapy to Alternative Drugs

After patients achieve adequate control of the heart rate and a stable clinical status, transition to alternative antiarrhythmic drugs may be accomplished.

When transitioning from BREVIBLOC to alternative drugs, the physician should carefully consider the labeling instructions of the alternative drug selected and reduce the dosage of BREVIBLOC as follows:

1. Thirty minutes following the first dose of the alternative drug, reduce the BREVIBLOC infusion rate by one-half (50%).
2. After administration of the second dose of the alternative drug, monitor the patient's response and if satisfactory control is maintained for the first hour, discontinue the BREVIBLOC infusion.

2.4 Directions for Use

BREVIBLOC injection is available in a pre-mixed bag and ready-to-use vial. BREVIBLOC is not compatible with Sodium Bicarbonate (5%) solution (limited stability) or furosemide (precipitation).

Parenteral drug products should be inspected visually for particulate matter and discoloration prior to administration, whenever solution and container permit.

Premixed Bag

- The medication port is to be used solely for withdrawing an initial bolus from the bag.
- Use aseptic technique when withdrawing the bolus dose.
- Do not add any additional medications to the bag.

Ready-to-Use Vial

The Ready-to-use Vial may be used to administer a loading dosage by hand-held syringe while the maintenance infusion is being prepared [see How Supplied/Storage and Handling (16.2)].

Compatibility with Commonly Used Intravenous Fluids

BREVIBLOC was tested for compatibility with ten commonly used intravenous fluids at a final concentration of 10 mg esmolol hydrochloride per mL. BREVIBLOC was found to be compatible with the following solutions and was stable for at least 24 hours at controlled room temperature or under refrigeration:

- Dextrose (5%) Injection, USP
- Dextrose (5%) in Lactated Ringer's Injection
- Dextrose (5%) in Ringer's Injection
- Dextrose (5%) and Sodium Chloride (0.45%) Injection, USP
- Dextrose (5%) and Sodium Chloride (0.9%) Injection, USP
- Lactated Ringer's Injection, USP
- Potassium Chloride (40 mEq/liter) in Dextrose (5%) Injection, USP
- Sodium Chloride (0.45%) Injection, USP
- Sodium Chloride (0.9%) Injection, USP

3 DOSAGE FORMS AND STRENGTHS

All BREVIBLOC dosage forms are iso-osmotic solutions of esmolol hydrochloride in sodium chloride.

4 CONTRAINDICATIONS

BREVIBLOC (Esmolol Hydrochloride) is contraindicated in patients with:

- Severe sinus bradycardia: May precipitate or worsen bradycardia resulting in cardiogenic shock and cardiac arrest [see Warnings and Precautions (5.2)].
- Heart block greater than first degree: Second- or third-degree atrioventricular block may precipitate or worsen bradycardia resulting in cardiogenic shock and cardiac arrest [see Warnings and Precautions (5.2)].
- Sick sinus syndrome: May precipitate or worsen bradycardia resulting in cardiogenic shock and cardiac arrest [see Warnings and Precautions (5.2)].
- Decompensated heart failure: May worsen heart failure.
- Cardiogenic shock: May precipitate further cardiovascular collapse and cause cardiac arrest.
- IV administration of cardiodepressant calcium-channel antagonists (e.g., verapamil) and BREVIBLOC in close proximity (i.e., while cardiac effects from the other are still present); fatal cardiac arrests have occurred in patients receiving BREVIBLOC and intravenous verapamil.
- Pulmonary hypertension: May precipitate cardiorespiratory compromise.
- Hypersensitivity reactions, including anaphylaxis to esmolol or any of the inactive ingredients of the product (cross-sensitivity between beta blockers is possible).

5 WARNINGS AND PRECAUTIONS

5.1 Hypotension

Hypotension can occur at any dose but is dose-related. Patients with hemodynamic compromise or on interacting medications are at particular risk. Severe reactions may include loss of consciousness, cardiac arrest, and death. For control of ventricular heart rate, maintenance doses greater than 200 mcg per kg per min are not recommended. Monitor patients closely, especially if pretreatment blood pressure is low. In case of an unacceptable drop in blood pressure, reduce or stop BREVIBLOC injection. Decrease of dose or termination of infusion reverses hypotension, usually within 30 minutes.

5.2 Bradycardia

Bradycardia, including sinus pause, heart block, severe bradycardia, and cardiac arrest have occurred with the use of BREVIBLOC injection. Patients with first-degree atrioventricular block, sinus node dysfunction, or conduction disorders may be at increased risk. Monitor heart rate and rhythm in patients receiving BREVIBLOC [see Contraindications (4)].

If severe bradycardia develops, reduce or stop BREVIBLOC.

5.3 Cardiac Failure

Beta blockers, like BREVIBLOC injection, can cause depression of myocardial contractility and may precipitate heart failure and cardiogenic shock. At the first sign or symptom of impending cardiac failure, stop BREVIBLOC and start supportive therapy [see Overdosage (10)].

5.4 Intraoperative and Postoperative Tachycardia and/or Hypertension

Monitor vital signs closely and titrate BREVIBLOC slowly in the treatment of patients whose blood pressure is primarily driven by vasoconstriction associated with hypothermia.

5.5 Reactive Airways Disease

Patients with reactive airways disease should, in general, not receive beta blockers. Because of its relative beta1 selectivity and titratability, titrate BREVIBLOC to the lowest possible effective dose. In the event of bronchospasm, stop the infusion immediately; a beta2 stimulating agent may be administered with appropriate monitoring of ventricular rates.

5.6 Use in Patients with Diabetes Mellitus and Hypoglycemia

In patients with hypoglycemia, or diabetic patients (especially those with labile diabetes) who are receiving insulin or other hypoglycemic agents, beta blockers may mask tachycardia occurring with hypoglycemia, but other manifestations such as dizziness and sweating may not be masked.

Concomitant use of beta blockers and antidiabetic agents can enhance the effect of antidiabetic agents (blood glucose-lowering).

5.7 Infusion Site Reactions

Infusion site reactions have occurred with the use of BREVIBLOC injection. They include irritation, inflammation, and severe reactions (thrombophlebitis, necrosis, and blistering), in particular when associated with extravasation [see Adverse Reactions (6)]. Avoid infusions into small veins or through a butterfly catheter.

If a local infusion site reaction develops, use an alternative infusion site and avoid extravasation.

5.8 Use in Patients with Prinzmetal's Angina

Beta blockers may exacerbate anginal attacks in patients with Prinzmetal's angina because of unopposed alpha receptor-mediated coronary artery vasoconstriction. Do not use nonselective beta blockers.

5.9 Use in Patients with Pheochromocytoma

If BREVIBLOC is used in the setting of pheochromocytoma, give it in combination with an alpha-blocker, and only after the alpha-blocker has been initiated. Administration of beta-blockers alone in the setting of pheochromocytoma has been associated with a paradoxical increase in blood pressure from the attenuation of beta-mediated vasodilation in skeletal muscle.

5.10 Use in Hypovolemic Patients

In hypovolemic patients, BREVIBLOC injection can attenuate reflex tachycardia and increase the risk of hypotension.

5.11 Use in Patients with Peripheral Circulatory Disorders

In patients with peripheral circulatory disorders (including Raynaud's disease or syndrome, and peripheral occlusive vascular disease), BREVIBLOC may aggravate peripheral circulatory disorders.

5.12 Abrupt Discontinuation of BREVIBLOC Injection

Severe exacerbations of angina, myocardial infarction, and ventricular arrhythmias have been reported in patients with coronary artery disease upon abrupt discontinuation of beta blocker therapy. Observe patients for signs of myocardial ischemia when discontinuing BREVIBLOC.

Heart rate increases moderately above pretreatment levels 30 minutes after BREVIBLOC discontinuation.

5.13 Hyperkalemia

Beta blockers, including BREVIBLOC, have been associated with increases in serum potassium levels and hyperkalemia. The risk is increased in patients with risk factors such as renal impairment. Intravenous administration of beta blockers has been reported to cause potentially life-threatening hyperkalemia in hemodialysis patients. Monitor serum electrolytes during therapy with BREVIBLOC.

5.14 Use in Patients with Metabolic Acidosis

Beta blockers, including BREVIBLOC, have been reported to cause hyperkalemic renal tubular acidosis. Acidosis in general may be associated with reduced cardiac contractility.

5.15 Use in Patients with Hyperthyroidism

Beta-adrenergic blockade may mask certain chemical signs (e.g., tachycardia) of hyperthyroidism. Abrupt withdrawal of beta blockade might precipitate a thyroid storm; therefore, monitor patients for signs of thyrotoxicosis when withdrawing beta blocking therapy.

5.16 Use in Patients at Risk of Severe Acute Hypersensitivity Reactions

When using beta blockers, patients at risk of anaphylactic reactions may be more reactive to allergen exposure (accidental, diagnostic, or therapeutic).

Patients using beta blockers may be unresponsive to the usual doses of epinephrine used to treat anaphylactic or anaphylactoid reactions [see Drug Interactions (7)].

6 ADVERSE REACTIONS

6.1 Clinical Trials Experience

Because clinical trials are conducted under widely varying conditions, adverse reaction rates observed in the clinical trials of a drug cannot be directly compared to rates in the clinical trials of another drug and may not reflect the rates observed in clinical practice.

The following adverse reaction rates are based on use of BREVIBLOC (Esmolol Hydrochloride) in clinical trials involving 369 patients with supraventricular tachycardia and over 600 intraoperative and postoperative patients enrolled in clinical trials. Most adverse effects observed in controlled clinical trial settings have been mild and transient. The most important and common adverse effect has been hypotension [see Warnings and Precautions (5.1)]. Deaths have been reported in post-marketing experience occurring during complex clinical states where BREVIBLOC was presumably being used to control ventricular rate [see Warnings and Precautions (5.5)].

Clinical Trial Adverse Reactions (Frequency <3%)

Psychiatric Disorders

Confusional state and agitation (~2%)

Anxiety, depression and abnormal thinking (<1%)

Nervous System Disorders

Headache (~ 2%)

Paresthesia, syncope, speech disorder, and lightheadedness (<1%)

Convulsions (<1%), with one death

Vascular Disorders

Peripheral ischemia (~1%)

Pallor and flushing (<1%)

Gastrointestinal Disorders

Vomiting (~1%)

Dyspepsia, constipation, dry mouth, and abdominal discomfort (<1%)

Renal and Urinary Disorders

Urinary retention (<1%)

6.2 Post-Marketing Experience

In addition to the adverse reactions reported in clinical trials, the following adverse reactions have been reported in the post-marketing experience. Because these reactions are reported voluntarily from a population of uncertain size, it is not always possible to estimate reliably their frequency or to establish a causal relationship to drug exposure.

Cardiac Disorders

Cardiac arrest, Coronary arteriospasm

Skin and Subcutaneous Tissue Disorders

Angioedema, Urticaria, Psoriasis

7 DRUG INTERACTIONS

Concomitant use of BREVIBLOC injection with other drugs that can lower blood pressure, reduce myocardial contractility, or interfere with sinus node function or electrical impulse propagation in the myocardium can exaggerate BREVIBLOC's effects on blood pressure, contractility, and impulse propagation. Severe interactions with such drugs can result in, for example, severe hypotension, cardiac failure, severe bradycardia, sinus pause, sinoatrial block, atrioventricular block, and/or cardiac arrest. In addition, with some drugs, beta blockade may precipitate increased withdrawal effects. (See clonidine, guanfacine, and monoxide below.) BREVIBLOC should therefore be used only after careful individual assessment of the risks and expected benefits in patients receiving drugs that can cause these types of pharmacodynamic interactions, including but not limited to:

- Digitalis glycosides: Concomitant administration of digoxin and BREVIBLOC leads to an approximate 10% to 20% increase of digoxin blood levels at some time points. Digoxin does not affect BREVIBLOC pharmacokinetics. Both digoxin and beta blockers slow atrioventricular conduction and decrease the heart rate. Concomitant use increases the risk of bradycardia.
- Anticholinesterases: BREVIBLOC prolonged the duration of succinylcholine-induced neuromuscular blockade and moderately prolonged clinical duration and recovery index of mivacurium.
- Antihypertensive agents clonidine, guanfacine, or moxonidine: Beta blockers also increase the risk of clonidine-, guanfacine-, or moxonidine-withdrawal rebound hypertension. If, during concomitant use of a beta blocker, antihypertensive therapy needs to be interrupted or discontinued, discontinue the beta blocker first, and the discontinuation should be gradual.
- Calcium channel antagonists: In patients with depressed myocardial function, use of BREVIBLOC with cardiodepressant calcium channel antagonists (e.g., verapamil) can lead to fatal cardiac arrests.
- Sympathomimetic drugs: Sympathomimetic drugs having beta-adrenergic agonist activity will counteract effects of BREVIBLOC.
- Vasoconstrictive and positive inotropic agents: Because of the risk of reducing cardiac contractility in presence of high systemic vascular resistance, do not use BREVIBLOC to control tachycardia in patients receiving drugs that are vasoconstrictive and have positive inotropic effects, such as epinephrine, norepinephrine, and dopamine.

8 USE IN SPECIFIC POPULATIONS

8.1 Pregnancy

Pregnancy Category C. Esmolol hydrochloride has been shown to produce increased fetal resorptions with minimal maternal toxicity in rabbits when given in doses approximately 8 times the maximum human maintenance dose (300 mcg/kg/min). There are no adequate and well-controlled studies in pregnant women. BREVIBLOC injection should be used during pregnancy only if the potential benefit justifies the potential risk to the fetus.

Teratogenicity studies in rats at intravenous dosages of esmolol hydrochloride up to 3000 mcg/kg/min (10 times the maximum human maintenance dosage) for 30 minutes daily produced no evidence of maternal toxicity, embryotoxicity or teratogenicity, while a dosage of 10,000 mcg/kg/min produced maternal toxicity and lethality. In rabbits, intravenous dosages up to 1000 mcg/kg/min for 30 minutes daily produced no evidence of maternal toxicity, embryotoxicity or teratogenicity, while 2500 mcg/kg/min produced minimal maternal toxicity and increased fetal resorptions.

8.2 Labor and Delivery

Although there are no adequate and well-controlled studies in pregnant women, use of esmolol in the last trimester of pregnancy or during labor or delivery has been reported to cause fetal bradycardia, which continued after termination of drug infusion. BREVIBLOC injection should be used during pregnancy only if the potential benefit justifies the potential risk to the fetus.

8.3 Nursing Mothers

It is not known whether this drug is excreted in human milk. Because many drugs are excreted in human milk and because of the potential for serious adverse reactions in nursing infants from BREVIBLOC, a decision should be made whether to discontinue nursing or to discontinue the drug, taking into account the importance of the drug to the mother.

8.4 Pediatric Use

The safety and effectiveness of BREVIBLOC in pediatric patients have not been established.

8.5 Geriatric Use

Clinical studies of BREVIBLOC injection did not include sufficient numbers of subjects aged 65 and over to determine whether they responded differently from younger subjects. Other reported clinical experience has not identified differences in responses between the elderly and younger patients. In general, dose selection for an elderly patient should usually start at the low end of the dosing range, reflecting greater frequency of decreased renal or cardiac function and of concomitant disease or other drug therapy.

8.6 Hepatic Impairment

No special precautions are necessary in patients with hepatic impairment because BREVIBLOC is metabolized by red-blood cell esterases [see Clinical Pharmacology (12)].

8.7 Renal Impairment

No dosage adjustment is required for esmolol in patients with renal impairment receiving a maintenance infusion of esmolol 150 mcg/kg for 4 hours. There is no information on the tolerability of maintenance infusions of esmolol using rates in excess of 150 mcg/kg or maintained longer than 4 hours [see Clinical Pharmacology (12)].

10 OVERDOSAGE

10.1 Signs and Symptoms of Overdose

Overdoses of BREVIBLOC (Esmolol Hydrochloride) can cause cardiac and central nervous system effects. These effects may precipitate severe signs, symptoms, sequelae, and complications (for example, severe cardiac and respiratory failure, including shock and coma), and may be fatal. Continuous monitoring of the patient is required.

- Cardiac effects include bradycardia, atrioventricular block (1st-, 2nd, 3rd degree), junctional rhythms, intraventricular conduction delays, decreased cardiac contractility, hypotension, cardiac failure (including cardiogenic shock), cardiac arrest/asystole, and pulseless electrical activity.
- Central nervous system effects include respiratory depression, seizures, sleep and mood disturbances, fatigue, lethargy, and coma.
- In addition, bronchospasm, mesenteric ischemia, peripheral cyanosis, hyperkalemia, and hypoglycemia (especially in children) may occur.

10.2 Treatment Recommendations

Because of its approximately 9-minute elimination half-life, the first step in the management of toxicity should be to discontinue the BREVIBLOC infusion. Then, based on the observed clinical effects, consider the following general measures.

Bradycardia

Consider intravenous administration of atropine or another anticholinergic drug or cardiac pacing.

Cardiac Failure

Consider intravenous administration of a diuretic or digitalis glycoside. In shock resulting from inadequate cardiac contractility, consider intravenous administration of dopamine, dobutamine, isoproterenol, or inamrinone. Glucagon has been reported to be useful.

Symptomatic hypotension

Consider intravenous administration of fluids or vasopressor agents such as dopamine or norepinephrine.

Bronchospasm

Consider intravenous administration of a beta2 stimulating agent or a theophylline derivative.

10.3 Dilution Errors

Massive accidental overdoses of BREVIBLOC have resulted from dilution errors. Use of BREVIBLOC PREMIXED Injection and BREVIBLOC DOUBLE STRENGTH PREMIXED Injection may reduce the potential for dilution errors. Some of these overdoses have been fatal while others resulted in permanent disability. Bolus doses in the range of 625 mg to 2.5 g (12.5-50 mg/kg) have been fatal. Patients have recovered completely from overdoses as high as 1.75 g given over one minute or doses of 7.5 g given over one hour for cardiovascular surgery. The patients who survived appear to be those whose circulation could be supported until the effects of BREVIBLOC resolved.

11 DESCRIPTION

BREVIBLOC (Esmolol Hydrochloride) is a beta adrenergic receptor blocker with a very short duration of action (elimination half-life is approximately 9 minutes). Esmolol hydrochloride is:

- (±)-Methyl p-[2-hydroxy-3-(isopropylamino) propoxy] hydrocinnamate hydrochloride and has the following structure:

- Esmolol hydrochloride has the empirical formula C16H26NO4Cl and a molecular weight of 331.8. It has one asymmetric center and exists as an enantiomeric pair.
- Esmolol hydrochloride is a white to off-white crystalline powder. It is a relatively hydrophilic compound which is very soluble in water and freely soluble in alcohol. Its partition coefficient (octanol/water) at pH 7.0 is 0.42 compared to 17.0 for propranolol.

11.1 BREVIBLOC Injection Dosage Forms

All BREVIBLOC presentations are clear, colorless to light yellow, sterile, nonpyrogenic, iso-osmotic solutions of esmolol hydrochloride in sodium chloride. The formulations for BREVIBLOC PREMIXED Injection, BREVIBLOC DOUBLE STRENGTH PREMIXED Injection, and BREVIBLOC Injection are described in the table below:

The calculated osmolarity of BREVIBLOC PREMIXED Injection and BREVIBLOC DOUBLE STRENGTH PREMIXED Injection is 312 mOsmol/L. The 250 mL and 100 mL bags are non-latex, non-PVC INTRAVIA bags with dual PVC ports. The INTRAVIA bags are manufactured from a specially designed multilayer plastic (PL 2408). Solutions in contact with the plastic container leach out certain chemical compounds from the plastic in very small amounts; however, biological testing was supportive of the safety of the plastic container materials.

12 CLINICAL PHARMACOLOGY

12.1 Mechanism of Action

BREVIBLOC (Esmolol Hydrochloride) is a beta1-selective (cardioselective) adrenergic receptor blocking agent with rapid onset, a very short duration of action, and no significant intrinsic sympathomimetic or membrane stabilizing activity at therapeutic dosages. Its elimination half-life after intravenous infusion is approximately 9 minutes. BREVIBLOC inhibits the beta1 receptors located chiefly in cardiac muscle, but this preferential effect is not absolute and at higher doses it begins to inhibit beta2 receptors located chiefly in the bronchial and vascular musculature.

12.2 Pharmacodynamics

Clinical pharmacology studies in normal volunteers have confirmed the beta blocking activity of BREVIBLOC, showing reduction in heart rate at rest and during exercise, and attenuation of isoprotenerol-induced increases in heart rate. Blood levels of BREVIBLOC have been shown to correlate with extent of beta blockade. After termination of infusion, substantial recovery from beta blockade is observed in 10-20 minutes. The acid metabolite of esmolol exhibits negligible pharmacological activity.

In human electrophysiology studies, BREVIBLOC produced effects typical of a beta blocker: a decrease in the heart rate, increase in sinus cycle length, prolongation of the sinus node recovery time, prolongation of the AH interval during normal sinus rhythm and during atrial pacing, and an increase in antegrade Wenckebach cycle length.

In patients undergoing radionuclide angiography, BREVIBLOC, at dosages of 200 mcg/kg/min, produced reductions in heart rate, systolic blood pressure, rate pressure product, left and right ventricular ejection fraction and cardiac index at rest, which were similar in magnitude to those produced by intravenous propranolol (4 mg). During exercise, BREVIBLOC produced reductions in heart rate, rate pressure product and cardiac index which were also similar to those produced by propranolol, but BREVIBLOC produced a significantly larger fall in systolic blood pressure. In patients undergoing cardiac catheterization, the maximum therapeutic dose of 300 mcg/kg/min of BREVIBLOC produced similar effects and, in addition, there were small, clinically insignificant increases in the left ventricular end diastolic pressure and pulmonary capillary wedge pressure. At 30 minutes after the discontinuation of BREVIBLOC infusion, all of the hemodynamic parameters had returned to pretreatment levels.

The relative cardioselectivity of BREVIBLOC was demonstrated in 10 mildly asthmatic patients. Infusions of BREVIBLOC 100, 200 and 300 mcg/kg/min produced no significant increases in specific airway resistance compared to placebo. At 300 mcg/kg/min, BREVIBLOC produced slightly enhanced bronchomotor sensitivity to dry air stimulus. These effects were not clinically significant, and BREVIBLOC was well tolerated by all patients. Six of the patients also received intravenous propranolol, and at a dosage of 1 mg, two experienced significant, symptomatic bronchospasm requiring bronchodilator treatment. One other propranolol-treated patient also experienced dry air-induced bronchospasm. No adverse pulmonary effects were observed in patients with COPD who received therapeutic dosages of BREVIBLOC for treatment of supraventricular tachycardia (51 patients) or in perioperative settings (32 patients).

12.3 Pharmacokinetics

Esmolol is rapidly metabolized by hydrolysis of the ester linkage, chiefly by the esterases in the cytosol of red blood cells and not by plasma cholinesterases or red cell membrane acetylcholinesterase. Total body clearance in man was found to be about 20 L/kg/hr, which is greater than cardiac output; thus the metabolism of esmolol is not limited by the rate of blood flow to metabolizing tissues such as the liver or affected by hepatic or renal blood flow. Esmolol has a rapid distribution half-life of about 2 minutes and an elimination half-life of about 9 minutes.

Using an appropriate loading dose, steady-state blood levels of BREVIBLOC for dosages from 50-300 mcg/kg/min are obtained within five minutes. Steady-state is reached in about 30 minutes without the loading dose. Steady-state blood levels of esmolol increase linearly over this dosage range and elimination kinetics are dose-independent over this range. Steady-state blood levels are maintained during infusion but decrease rapidly after termination of the infusion. Because of its short half-life, blood levels of esmolol can be rapidly altered by increasing or decreasing the infusion rate and rapidly eliminated by discontinuing the infusion.

Consistent with the high rate of blood-based metabolism of esmolol, less than 2% of the drug is excreted unchanged in the urine. Within 24 hours of the end of infusion, the acid metabolite of esmolol in urine accounts for approximately 73-88% of the dosage.

Metabolism of esmolol results in the formation of the corresponding free acid and methanol. The acid metabolite has been shown in animals to have negligible activity and in normal volunteers its blood levels do not correspond to the level of beta blockade. The acid metabolite has an elimination half-life of about 3.7 hours and is excreted in the urine with a clearance approximately equivalent tot he glomerular filtration rate. After a 4 hour maintenance infusion of 150 mcg/kg, the plasma concentrations of esmolol are similar in subjects with normal renal function and in patients with ESRD on dialysis. The half-life of the acid metabolite of BREVIBLOC, which is primarily excreted unchanged by the kidney, is increased about 12-fold to 48 hours in patients with ESRD. The peak concentrations of the acid metabolite are doubled in ESRD.

Methanol blood levels, monitored in subjects receiving BREVIBLOC for up to 6 hours at 300 mcg/kg/min and 24 hours at 150 mcg/kg/min, approximated endogenous levels and were less than 2% of levels usually associated with methanol toxicity.

BREVIBLOC has been shown to be 55% bound to human plasma protein, while the acid metabolite is only 10% bound.

13 NONCLINICAL TOXICOLOGY

Because of its short term usage no carcinogenicity, mutagenicity, or reproductive performance studies have been conducted with esmolol.

14 CLINICAL STUDIES

Supraventricular Tachycardia

In two multicenter, randomized, double-blind, controlled comparisons of BREVIBLOC injection with placebo and propranolol, maintenance doses of 50 to 300 mcg/kg/min of BREVIBLOC were found to be more effective than placebo and about as effective as propranolol, 3-6 mg given by bolus injections, in the treatment of supraventricular tachycardia, principally atrial fibrillation and atrial flutter. The majority of these patients developed their arrhythmias postoperatively. After 60-70% of the patients treated with BREVIBLOC developed either a 20% reduction in heart rate, a decrease in heart rate to less than 100 bpm, or, rarely, conversion to normal sinus rhythm and about 95% of these patients did so at a dosage of 200 mcg/kg/min or less. The average effective dosage of BREVIBLOC was approximately 100 mcg/kg/min in the two studies. Other multicenter baseline-controlled studies gave similar results. In the comparison with propranolol, about 50% of patients in both the BREVIBLOC and propranolol groups were on concomitant digoxin. Response rates were slightly higher with both beta blockers in the digoxin-treated patients.

In all studies significant decreases of blood pressure occurred in 20-50% of patients, identified either as adverse reaction reports by investigators, or by observation of systolic pressure less than 90 mmHg or diastolic pressure less than 50 mmHg. The hypotension was symptomatic (mainly hyperhidrosis or dizziness) in about 12% of patients, and therapy was discontinued in about 11% of patients, about half of whom were symptomatic. Hypotension was more common with BREVIBLOC (53%) than with propranolol (17%). The hypotension was rapidly reversible with decreased infusion rate or after discontinuation of therapy with BREVIBLOC. For both BREVIBLOC and propranolol, hypotension was reported less frequently in patients receiving concomitant digoxin.

16 HOW SUPPLIED/STORAGE AND HANDLING

16.1 How Supplied

BREVIBLOC PREMIXED Injection

- NDC 10019-055-61, 2500 mg / 250 mL (10 mg/mL) Ready-to-use INTRAVIA Bags

BREVIBLOC DOUBLE STRENGTH PREMIXED Injection

- NDC 10019-075-87, 2000 mg / 100 mL (20 mg/mL) Ready-to-use INTRAVIA Bags

BREVIBLOC Injection

- NDC 10019-115-01, 100 mg / 10 mL (10 mg/mL) Ready-to-use Vials, Package of 25

Product repackaged by: Henry Schein, Inc., Bastian, VA 24314
From Original Manufacturer/Distributor's NDC and Unit of Sale | To Henry Schein Repackaged Product NDC and Unit of Sale | Total Strength/Total Volume (Concentration) per unit
NDC 10019-115-01 Ready-to-use Vials, Package of 25 | NDC 0404-9825-10 1 Vial in a bag (Vial bears NDC 10019-115-39) | 100 mg/10 mL (10 mg/mL)

16.2 Storage

Store at 25°C (77°F). Excursions permitted to 15°-30°C (59°-86°F) [see USP Controlled Room Temperature]. Protect from freezing. Avoid excessive heat.

Each bag contains no preservative. Once drug has been withdrawn from ready-to-use bag, the bag should be used within 24 hours, with any unused portion discarded.

Do not use plastic containers in series connections. Such use could result in an embolism due to residual air being drawn from the primary container before administration of the fluid from the secondary container is completed.

Do not remove unit from overwrap until ready to use. Do not use if overwrap has been previously opened or damaged. The overwrap is a moisture barrier. The inner bag maintains sterility of the solution. Tear overwrap at notch and remove premixed bag. Some opacity of the plastic due to moisture absorption during the sterilization process may be observed. This is normal and does not affect the solution quality or safety. The opacity will diminish gradually.

Check for minute leaks by squeezing the inner bag firmly. If leaks are found, discard solution, as sterility may be impaired. Do not use unless the solution is clear (colorless to light yellow) and the seal is intact.

Preparation for intravenous administration:

- Use aseptic technique
- Suspend premixed bag from eyelet support.
- Remove plastic protector from delivery port at bottom of bag.
- Attach administration set.
- Refer to complete directions accompanying set.